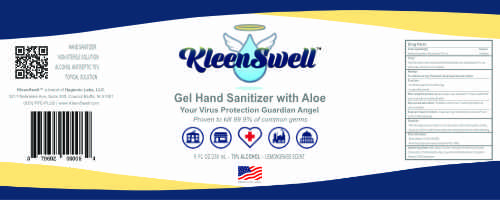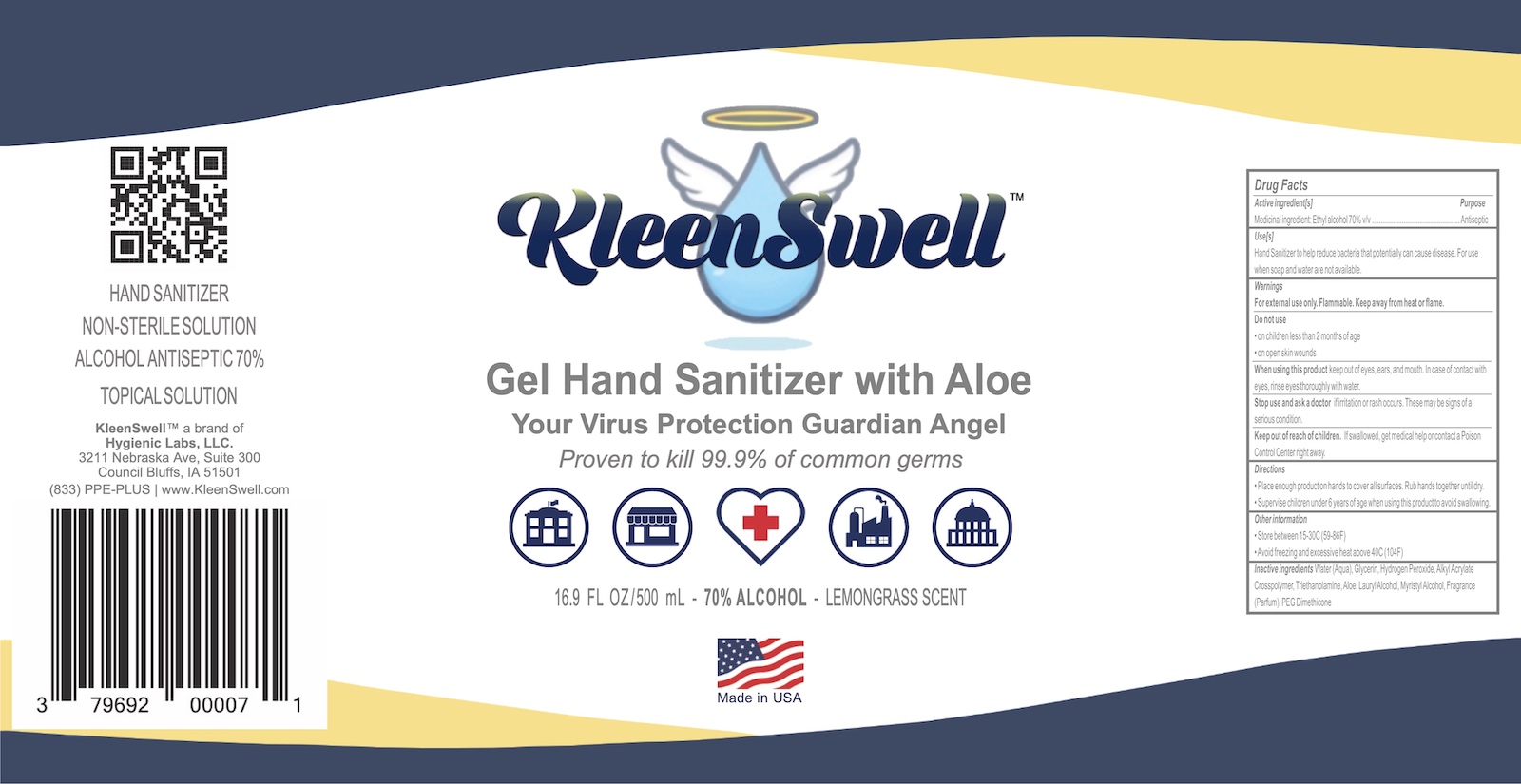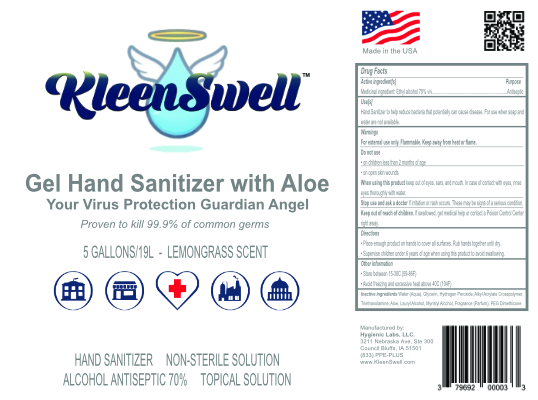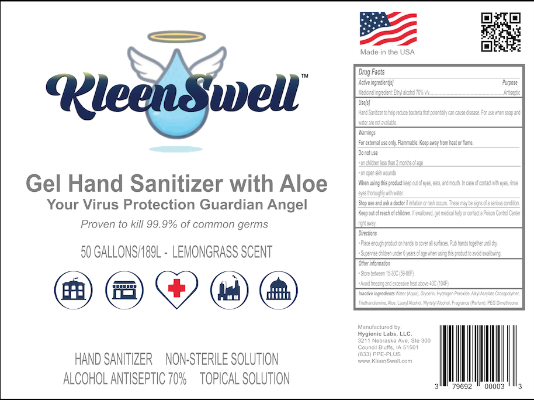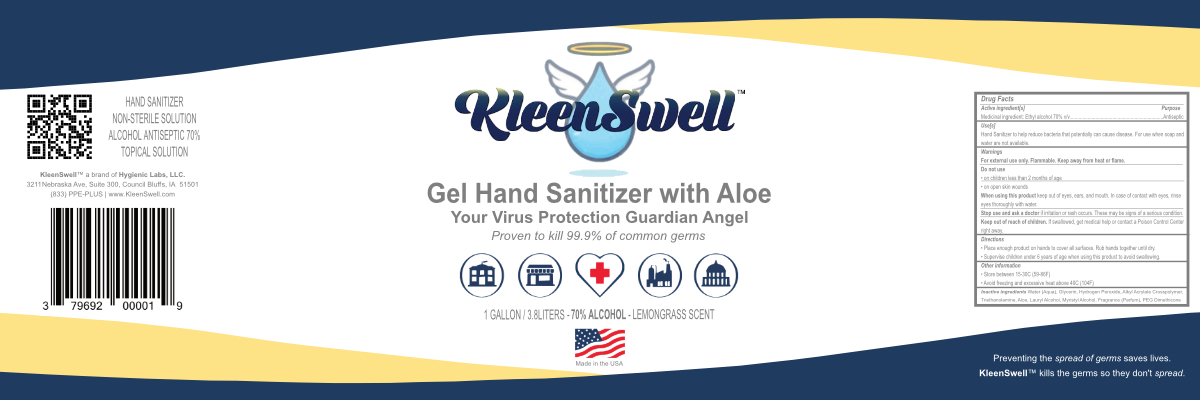 DRUG LABEL: KleenSwell Gel Hand Sanitizer
NDC: 79692-003 | Form: GEL
Manufacturer: Hygienic Labs, LLC.
Category: otc | Type: HUMAN OTC DRUG LABEL
Date: 20201211

ACTIVE INGREDIENTS: ALCOHOL 70.6586 mL/100 mL
INACTIVE INGREDIENTS: TROLAMINE 0.6023 mL/100 mL; WEST INDIAN LEMONGRASS OIL 0.0187 mL/100 mL; ALOE VERA LEAF 0.2665 mL/100 mL; HYDROGEN PEROXIDE 0.1258 mL/100 mL; METHACRYLIC ACID - ETHYL ACRYLATE COPOLYMER (4500 MPA.S) 7.6152 mL/100 mL; PEG-10 DIMETHICONE (600 CST) 0.0216 mL/100 mL; MYRISTYL LACTATE 0.2656 mL/100 mL; WATER; GLYCERIN 1.3344 mL/100 mL

KLEENSWELL GEL HAND SANITIZER - 70% alcohol gel
Hygienic Labs, LLC.

Disclaimer: Most OTC drugs are not reviewed and approved by FDA, however they may be marketed if they comply with applicable regulations and policies. FDA has not evaluated whether this product complies.

----------

This is hand sanitizer is manufactured using United States Pharmacopoeia (USP) grade ingredients in the preparation of the product (percentage in final product formulation).

Active Ingredients

Medicinal ingredient: Ethyl alcohol 70% v/v............... Purpose: Antiseptic

Purpose

Antiseptic, Hand Sanitizer

Use

Hand Sanitizer to help reduce viruses and bacteria that potentially can cause disease. For use when soap and water are not available.

Warnings

For external use only. Flammable. Keep away from heat or flame.

Do Not Use

- in children less than 2 months of age
- on open skin wounds

When using this product keep out of eyes, ears, and mouth. In case of contact with eyes, rinse eyes thoroughly with water.

Stop use and ask a doctor if irritation or rash occurs. These may be signs of a serious condition.

Keep out of reach of children. If swallowed, get medical help or contact a Poison Control Center right away.

Directions

Place enough product on hands to cover all surfaces. Rub hands together until dry.
Supervise children under 6 years of age when using this product to avoid swallowing.

Other Information

- Store between 15-30C (59-86F)
- Avoid freezing and excessive heat above 40C (104F)

INACTIVE INGREDIENT

Water (Aqua), Glycerin, Hydrogen Peroxide, Alkyl Acrylate Crosspolymer, Triethanolamine, Aloe, Lauryl Alcohol, Myristyl Alcohol, Fragrance (Parfum), PEG Dimethicone

RECENT MAJOR CHANGES

Dosage and Administration Section was added

Package Label - Principal Product Label

3800 mL NDC: 79692-003-01

19000 mL NDC: 79692-003-05

189000 mL NDC: 79692-003-50

250 mL NDC: 79692-003-08

500 mL NDC: 79692-003-16